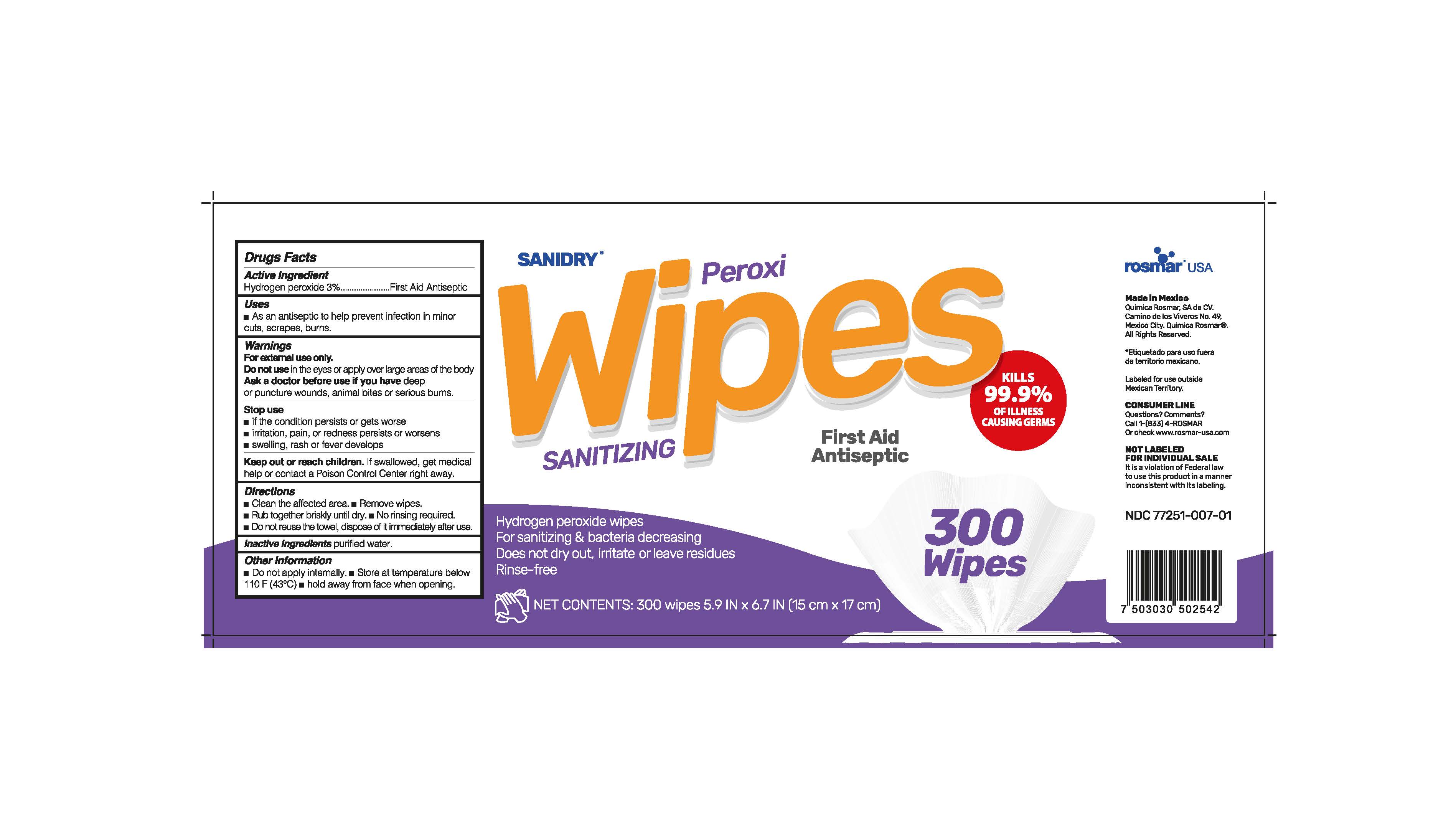 DRUG LABEL: Sanidry
NDC: 77251-007 | Form: CLOTH
Manufacturer: QUIMICA ROSMAR S.A DE C.V
Category: otc | Type: HUMAN OTC DRUG LABEL
Date: 20210118

ACTIVE INGREDIENTS: HYDROGEN PEROXIDE 3 mL/100 mL
INACTIVE INGREDIENTS: WATER

77251-007 Sanidry
Hydrogen Peroxide 3%

This is a hand sanitizer manufactured according to the Temporary Policy for Preparation of Certain Alcohol-Based Hand Sanitizer Products During the Public Health Emergency (CoViD-19); Guidance for Industry.

The hand sanitizer is manufactured using only the following United States Pharmacopoeia (USP) grade ingredients in the preparation of the product (percentage in final product formulation) consistent with World Health Organization (WHO) recommendations:

1. Alcohol (ethanol) (USP or Food Chemical Codex (FCC) grade) (80%, volume/volume (v/v)) in an aqueous solution denatured according to Alcohol and Tobacco Tax and Trade Bureau regulations in 27 CFR part 20.
2. Glycerol (1.45% v/v).
3. Hydrogen peroxide (0.125% v/v).
4. Sterile distilled water or boiled cold water.

The firm does not add other active or inactive ingredients. Different or additional ingredients may impact the quality and potency of the product.

Active Ingredient(s)

Hydrogen peroxide 3% v/v. Purpose: First Aid Antiseptic

Purpose

First Aid Antiseptic

Use

As an antiseptic to help prevent infection in minor cuts, scrapes, burns.

Warnings

For external use only.

Do not use in the eyes or apply over large areas of the body

Ask a doctor before use if you have deep or puncture wounds, animal bites or serious burns.

When using this product keep out of eyes, ears, and mouth. In case of contact with eyes, rinse eyes thoroughly with water.
Stop use and ask a doctor if irritation or rash occurs. These may be signs of a serious condition.
Keep out of reach of children. If swallowed, get medical help or contact a Poison Control Center right away.

Stop use

- if the condition persists or gets worse
- irritation, pain or redness persists or worsens
- swelling, rash or fever develops

Keep out of reach of children. If swallowed, get medical help or contact a Poison Control Center right away.

Directions

- Clean the affected area
- Remove wipes
- Rub together briskly until dry
- No rinsing required
- Do not reuse the towel, dispose immediately after use.

Other information

- Do not apply internally
- Store at temperature below 110F(43C)
- Hold away from face when opening

Inactive ingredients

purified water

Package Label - Principal Display Panel

300 units NDC: 77251-007-01 -000-00